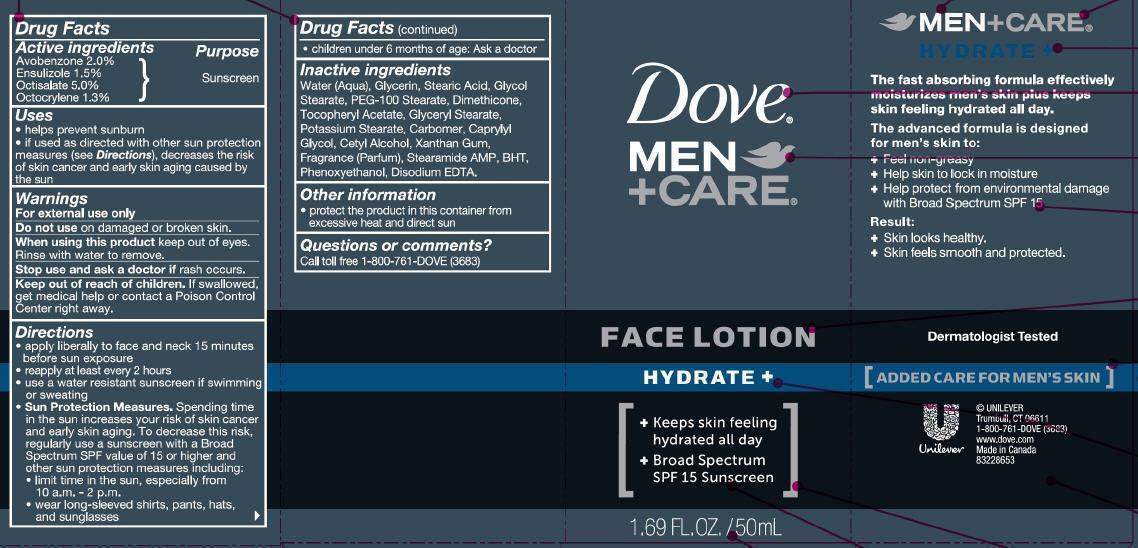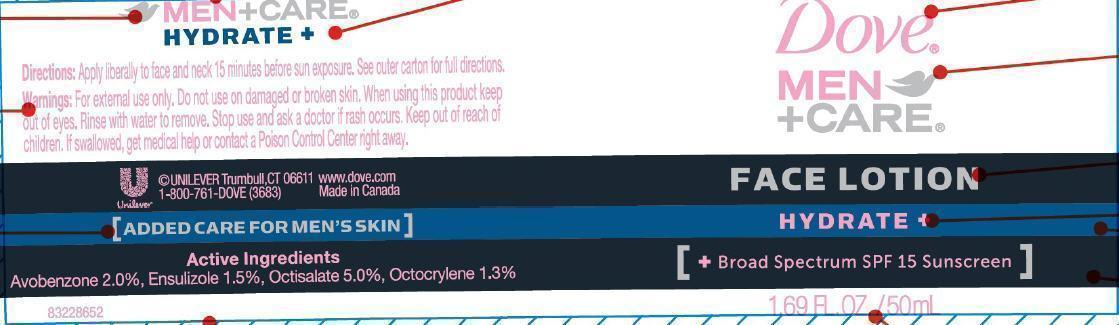 DRUG LABEL: Dove
NDC: 64942-1334 | Form: LOTION
Manufacturer: CONOPCO Inc. d/b/a Unilever
Category: otc | Type: HUMAN OTC DRUG LABEL
Date: 20241107

ACTIVE INGREDIENTS: AVOBENZONE 2 g/100 mL; ENSULIZOLE 1.5 g/100 mL; OCTISALATE 5 g/100 mL; OCTOCRYLENE 1.3 g/100 mL
INACTIVE INGREDIENTS: GLYCERYL MONOSTEARATE; CAPRYLYL GLYCOL; CETYL ALCOHOL; XANTHAN GUM; STEARAMIDE AMP; BUTYLATED HYDROXYTOLUENE; PHENOXYETHANOL; EDETATE DISODIUM; WATER; GLYCERIN; STEARIC ACID; GLYCOL STEARATE; PEG-100 STEARATE; DIMETHICONE; .ALPHA.-TOCOPHEROL ACETATE; POTASSIUM STEARATE

Dove Men plus Care Hydrate Face Lotion SPF 15

Active Ingredients
Avobenzone (2.0%)
Ensulizole (1.5%)
Octisalate (5.0%)

Octocrylene (1.3%)

Purpose
Sunscreen

Uses

· helps prevent sunburn
· if used as directed with other sun protection measures (see Directions), decreases the risk of skin cancer and early skin aging caused by the sun

Warnings

For external use only

Do not use on damaged or broken skin.

When using this product keep out of eyes. Rinse with water to remove.

Stop use and ask a doctor if rash occurs.

Keep out of reach of children. If swallowed, get medical help or contact a Poison Control Center right away.

DOSAGE AND ADMINISTRATION

Directions· apply liberally to face and neck 15 minutes before sun exposure
· reapply at least every 2 hours
· use a water resistant sunscreen if swimming or sweating
Sun Protection Measures. Spending time in the sun increases your risk of skin cancer and early skin aging. To decrease this risk, regularly use a sunscreen with a Broad Spectrum SPF value of 15 or higher and other sun protection measures including:
· limit time in the sun, especially from 10a.m. - 2p.m.
· wear long-sleeved shirts, pants, hats, and sunglasses

· children under 6 months of age; ask a doctor

Inactive ingredients

Water (Aqua), Glycerin, Stearic Acid, Glycol Stearate, PEG-100 Stearate, Dimethicone, Tocopheryl Acetate, Glyceryl Stearate, Potassium Stearate, Carbomer, Caprylyl Glycol, Cetyl Alcohol, Xanthan Gum, Fragrance (Parfum), Stearamide AMP, BHT, Phenoxyethanol, Disodium EDTA

Questions or comments?
Call toll free 1-800-761-DOVE (3683)